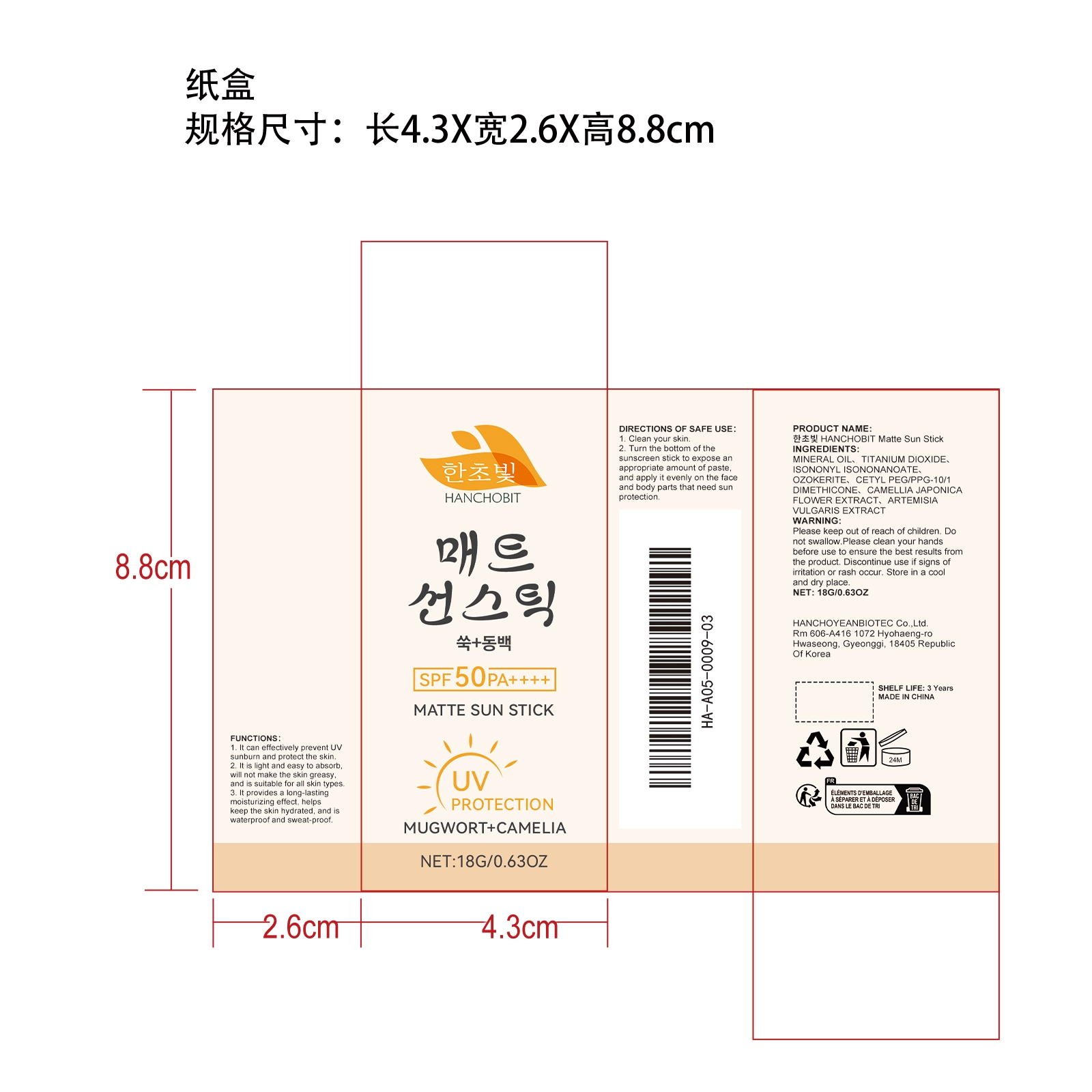 DRUG LABEL: HANCHOBIT Matte Sun Stick
NDC: 85164-004 | Form: CREAM
Manufacturer: HANCHOYEANBIOTEC Co.,Ltd.
Category: otc | Type: HUMAN OTC DRUG LABEL
Date: 20251127

ACTIVE INGREDIENTS: ARTEMISIA VULGARIS ROOT 0.0036 mg/18 mg; CAMELLIA JAPONICA FLOWER 0.0036 mg/18 mg
INACTIVE INGREDIENTS: MINERAL OIL 7.4628 mg/18 mg; TITANIUM DIOXIDE 4.5 mg/18 mg; CERESIN 3.6 mg/18 mg; ISONONYL ISONONANOATE 1.8 mg/18 mg; CETYL PEG/PPG-10/1 DIMETHICONE (HLB 2) 0.63 mg/18 mg

ACTIVE INGREDIENT

CAMELLIA JAPONICA FLOWER EXTRACT、ARTEMISIA VULGARIS EXTRACT

WHEN USING

1. Clean your skin.

2. Turn the bottom of the sunscreen stick to expose an appropriate amount of paste, and apply it evenly on the face and body parts that need sun protection.

PURPOSE

1. It can effectively prevent UV sunburn and protect the skin.

2. It is light and easy to absorb, will not make the skin greasy, and is suitable for all skin types.

3. It provides a long-lasting moisturizing effect, helps keep the skin hydrated, and is waterproof and sweat-proof.

WARNINGS

Please keep out of reach of children. Do not swallow.Please clean your hands before use to ensure the best results from the product. Discontinue use if signs of irritation or rash occur. Store in a cool and dry place.

DO NOT USE

Discontinue use if signs of irritation or rash occur.

STOP USE

Discontinue use if signs of irritation or rash occur.

KEEP OUT OF REACH OF CHILDREN

Please keep out of reach of children. Do not swallow.

STORAGE AND HANDLING

Store in a cool and dry place.

INACTIVE INGREDIENT

MINERAL OIL、TITANIUM DIOXIDE、ISONONYL ISONONANOATE、OZOKERITE、CETYL PEG/PPG-10/1 DIMETHICONE